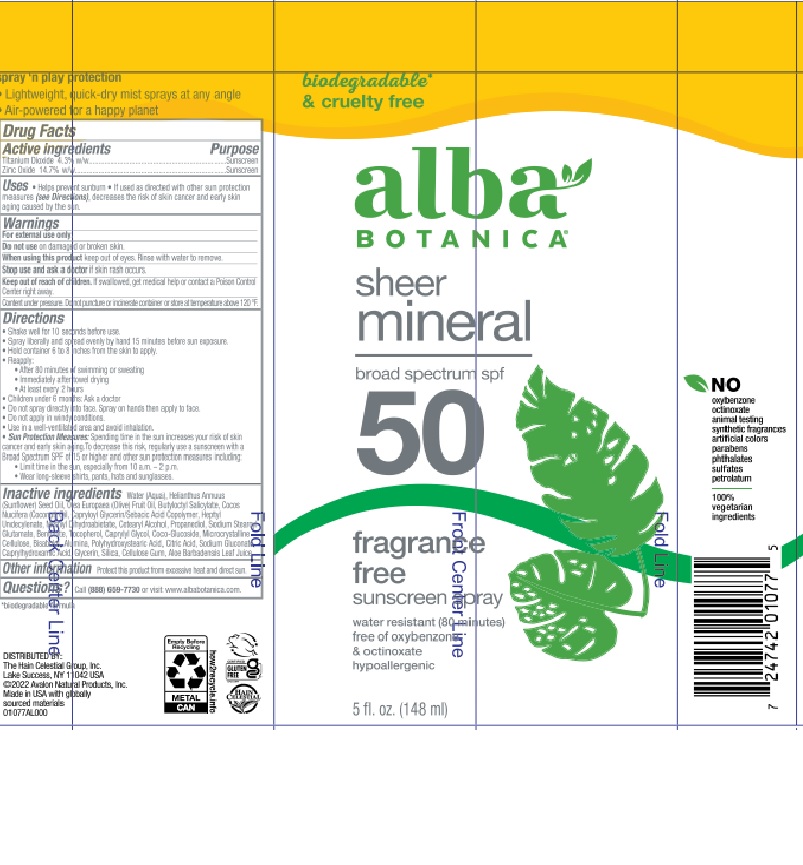 DRUG LABEL: Alba Botanica Sheer Mineral SPF 50
NDC: 61995-3032 | Form: AEROSOL
Manufacturer: The Hain Celestial Group, Inc.
Category: otc | Type: HUMAN OTC DRUG LABEL
Date: 20241128

ACTIVE INGREDIENTS: ZINC OXIDE 14.7 g/100 g; TITANIUM DIOXIDE 4.3 g/100 g
INACTIVE INGREDIENTS: WATER; GLYCERIN; .ALPHA.-TOCOPHEROL ACETATE; POLYHYDROXYSTEARIC ACID (2300 MW); SODIUM GLUCONATE; COCO GLUCOSIDE; SUNFLOWER OIL; CAPRYLYL GLYCOL; PROPANEDIOL; CELLULOSE, MICROCRYSTALLINE; .BETA.-BISABOLOL; CAPRYLOYL GLYCERIN/SEBACIC ACID COPOLYMER (2000 MPA.S); CAPRYLHYDROXAMIC ACID; SILICON DIOXIDE; BUTYLOCTYL SALICYLATE; ANHYDROUS CITRIC ACID; METHYL DIHYDROABIETATE; OLIVE OIL; COCONUT OIL; HEPTYL UNDECYLENATE; CARBOXYMETHYLCELLULOSE; ALOE VERA LEAF; CETEARYL GLUCOSIDE; SODIUM STEAROYL GLUTAMATE; BENTONITE; ALUMINUM OXIDE

Alba Botanica Sheer Minieal SPF 50

ACTIVE INGREDIENT

Zinc Oxide 14.7% (w/w)

Titanium Dioxide 4.3% (w/w)

DOSAGE AND ADMINISTRATION

Apply liberally 15 minutes before sun exposure. Reapply: ● after 80 minutes of swimming or sweating ● immediately after towel drying ● at least every 2 hours. Children under 6 months of age: ask a doctor.

PURPOSE

Sunscreen

WARNINGS

For external use only. Do not use on damaged or broken skin. When using this product keep out of eyes. Rinse with water to remove. Stop use and ask a doctor if skin rash occurs.

Keep out of reach of children. If swallowed get medical help or contact Poison Center right away.

INACTIVE INGREDIENT

Water (Aqua), Helianthus Annuus (Sunflower) Seed Oil, Olea Europaea (Olive) Fruit Oil, Butyloctyl Salicylate, Cocos Nucifera (Coconut) Oil, Capryloyl Glycerin/Sebacic Acid Copolymer, Heptyl Undecylenate, Methyl Dihydrobietate, Cetearyl Alcohol, Propanediol, Sodium Stearoyl Glutamate, Bentonite, Tocopherol, Caprylyl Glycol, Coco-Glucoside, Microcrystalline Cellulose, Bisabolol, Alumina, Polyhydroxystearic Acid, Citric Acid, Sodium Gluconate, Caprylhydroxamic Acid, Glycerin, Silica, Cellulose Gum, Aloe Barbadensis Leaf Juice

INDICATIONS AND USAGE

Helps prevents sunburns. If used as directed with other sun protection measures, decreases risk of skin cancer and early skin aging caused by sun exposure. Skin Protection Measures: Spending time in the sun increases your risk of skin cancer and early skin aging. To decrease risk, regularly use sunscreen with Broad Spectrum SPF 15 or higher and other protective measures including: limit time in sun, especially from10am to 2pm, and wear long sleeved shirts, pants, hats and sunglases.